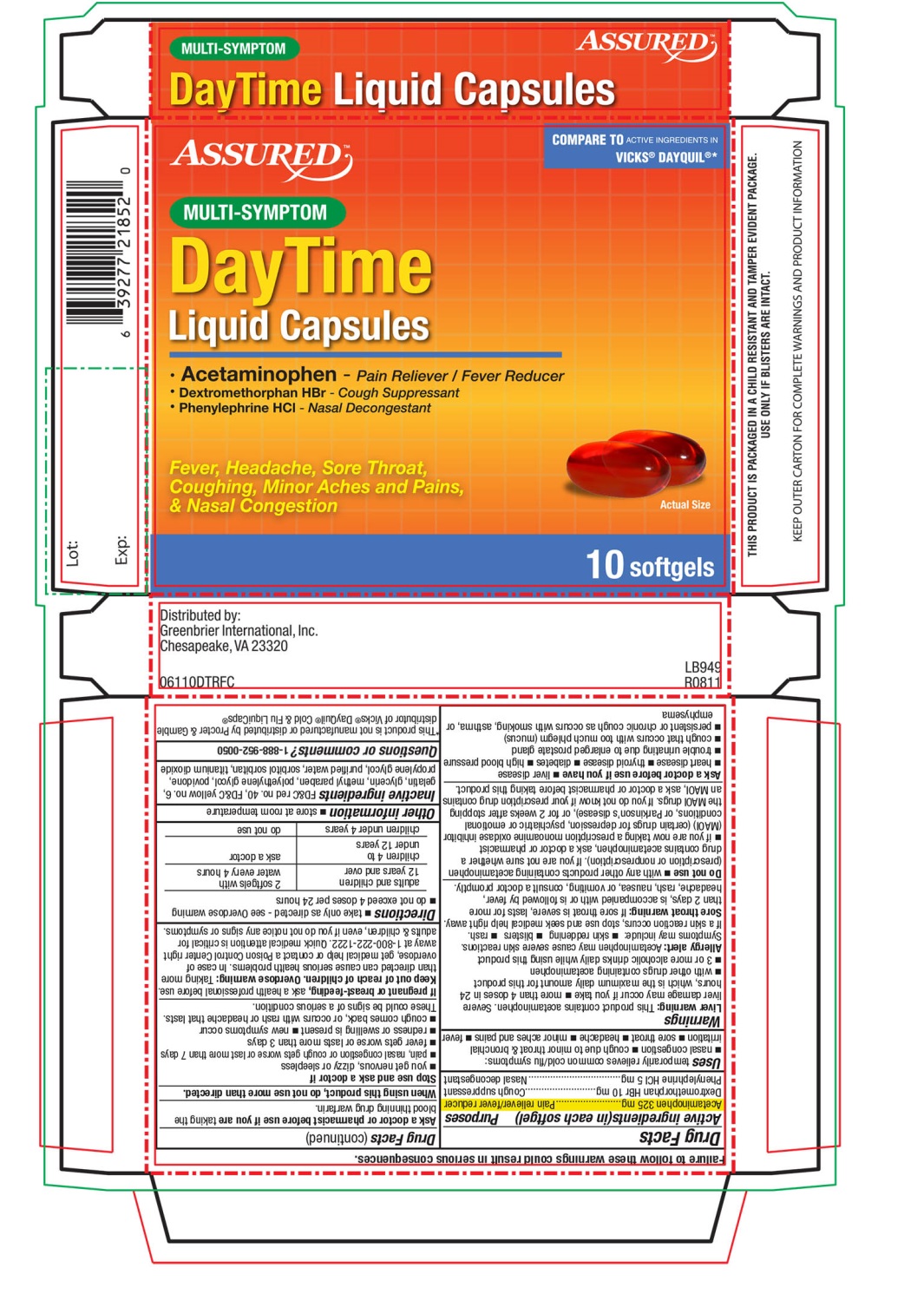 DRUG LABEL: Multi Symptom Daytime
NDC: 33992-6110 | Form: CAPSULE, LIQUID FILLED
Manufacturer: Greenbrier International, Inc.
Category: otc | Type: HUMAN OTC DRUG LABEL
Date: 20171227

ACTIVE INGREDIENTS: ACETAMINOPHEN 325 mg/1 1; Dextromethorphan Hydrobromide 10 mg/1 1; Phenylephrine Hydrochloride 5 mg/1 1
INACTIVE INGREDIENTS: FD&C Red No. 40; FD&C Yellow No. 6; gelatin; glycerin; METHYLPARABEN; polyethylene glycols; POVIDONES; propylene glycol; water; sorbitol; titanium dioxide

Multi-Symptom Daytime Liquid Capsules 10 softgels

Drug Facts

Active ingredients

BOXED WARNING

Active ingredients (in each softgel)

Acetaminophen 325 mg

Dextromethorphan HBr 10 mg

Phenylephrine HCl 5 mg

Purposes

Purposes

Pain reliever/fever reducer

Cough suppressant

Nasal decongestant

Uses

temporarily relieves common cold/flu symptoms:

- nasal congestion
- cough due to minor throat & bronchial irritation
- sore throat
- headache
- minor aches & pains
- fever

Warnings

Liver warning

This product contains acetaminophen. Severe liver damage may occur if you take

- more than 4 doses in 24 hours, which is the maximum daily amount for this product
- with other drugs containing acetaminophen
- 3 or more alcoholic drinks daily while using this product

Allergy alert

Acetaminophen may cause severe skin reactions. Symptoms may include:
●skin reddening● blisters● rash
If a skin reaction occurs, stop use and seek medical help right away.

Sore throat warning

If sore throat is severe, lasts for more than 2 days, occurs with or is followed by fever, headache, rash, nausea, or vomiting, see a doctor promptly.

Do not use

- with any other drug containing acetaminophen (prescription or nonprescription). If you are not sure whether a drug contains acetaminophen, ask a doctor or pharmacist.
- if you are now taking a prescription monoamine oxidase inhibitor (MAOI) (certain drugs for depression, psychiatric or emotional conditions, or Parkinson's disease), or for 2 weeks after stopping the MAOI drug. If you do not know if your prescription drug contains an MAOI, ask a doctor or pharmacist before taking this product.

Ask a doctor before use if you have

- liver disease
- heart disease
- thyroid disease
- diabetes
- high blood pressure
- trouble urinating due to enlarged prostate gland
- cough that occurs with too much phlegm (mucus)
- persistent or chronic cough as occurs with smoking, asthma, or emphysema

Ask a doctor or pharmacist before use if you are taking the blood thinning drug warfarin.

When using this product, do not use more than directed.

Stop use and ask a doctor if

- you get nervous, dizzy or sleepless
- pain, nasal congestion or cough get worse or last more than 7 days
- fever gets worse or lasts more than 3 days
- redness or swelling is present
- new symptoms occur
- cough comes back, or occurs with rash or headache that lasts. These could be signs of a serious condition.

PREGNANCY OR BREAST FEEDING

If pregnant or breast-feeding, ask a health professional before use.

Keep out of reach of children.

Overdose warning

Taking more than directed can cause serious health problems. In case of overdose, get medical help or contact a Poison Control Center right away. Quick medical attention is critical for adults & for children even if you do not notice any signs or symptoms.

Directions

- take only as directed - see Overdose Warning
- do not exceed 4 doses per 24 hours

adults & children 12 years and over | 2 Softgels with water every 4 hours
children 4 to under 12 years | ask a doctor
children under 4 years | do not use

Other information

- store at room temperature

Inactive ingredients

FD&C Red No. 40, FD&C Yellow No. 6, gelatin, glycerin, methyl paraben, polyethylene glycol, povidone, propylene glycol, purified water, sorbitol sorbitan, titanium dioxide

Questions or comments?

1-888-952-0050

Distributed by:

Greenbrier International, Inc.

Chesapeake, VA 23320

PRINCIPAL DISPLAY PANEL - 10 Softgel Carton

ASSURED

COMPARE TO ACTIVE INGREDIENTS IN VICKS ®DAYQUIL®

Multi-Symptom

DayTime

Liquid Capsules

- Acetaminophen- Pain Reliever/Fever Reducer
- Dextromethorphan HBr- Cough Suppressant
- Phenylephrine HCl -Nasal Decongestant

Fever, Headache, Sore Throat, Coughing, Minor Aches and Pains, & Nasal congestion

10 Softgels

COMPARE TO ACTIVE INGREDIENT IN VICKS DAYQUIL®

THIS PRODUCT IS PACKAGED IN A CHILD RESISTANT AND TAMPER EVIDENT PACKAGE. USE ONLY IF BLISTERS ARE INTACT.

KEEP OUTER CARTON FOR COMPLETE WARNINGS AND PRODUCT INFORMATION

*This product is not manufactured or distributed by Procter & Gamble distributor of Vicks®DayQuil® Cold &Flu LiquiCaps®